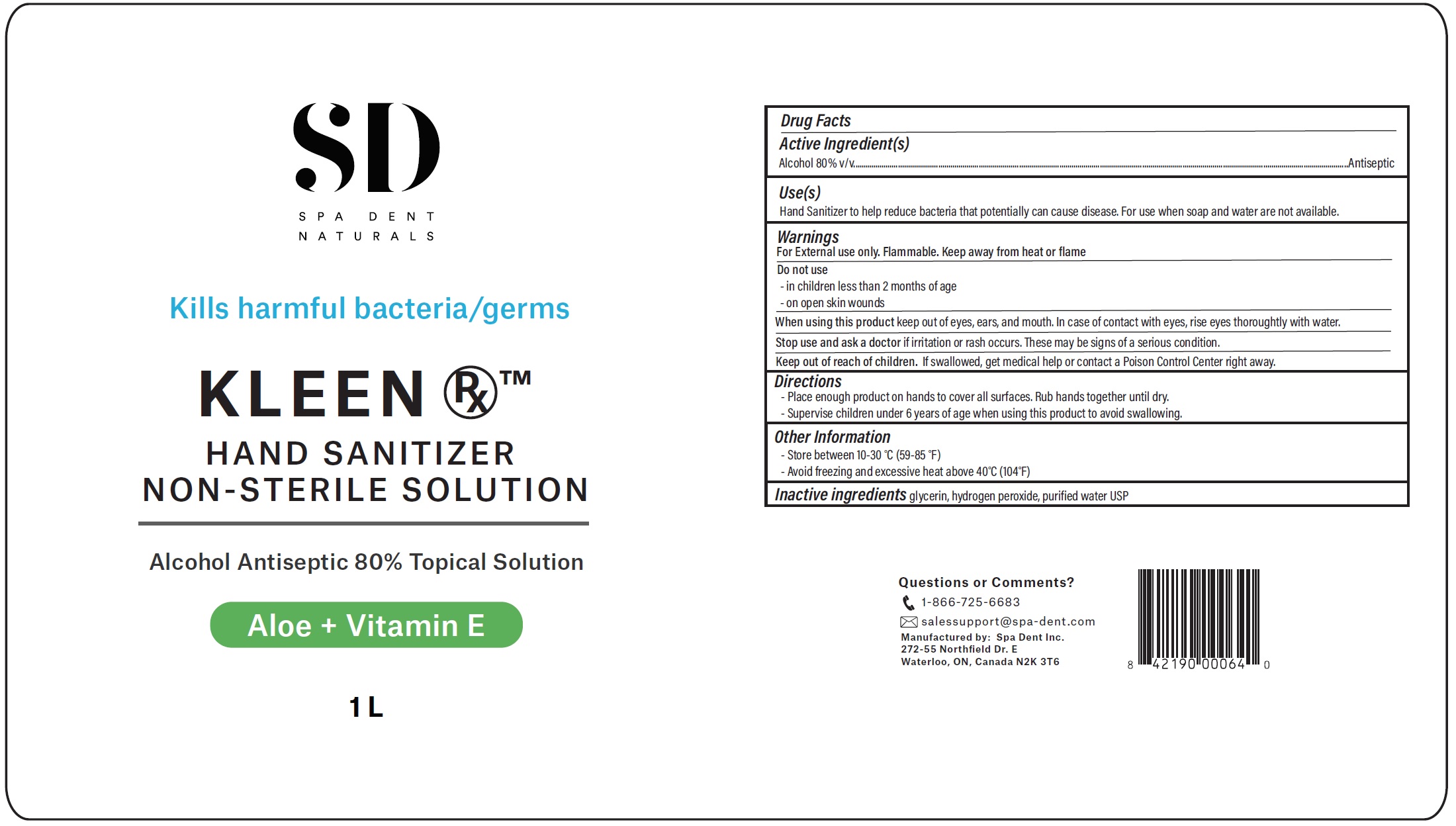 DRUG LABEL: SD KLEEN RX HAND SANITIZER
NDC: 79147-001 | Form: SOLUTION
Manufacturer: Spa Dent Inc.
Category: otc | Type: HUMAN OTC DRUG LABEL
Date: 20200717

ACTIVE INGREDIENTS: ALCOHOL 0.8 mL/1 mL
INACTIVE INGREDIENTS: GLYCERIN; HYDROGEN PEROXIDE; WATER

SD KLEEN RX HAND SANITIZER

Active Ingredient(s)

Alcohol 80% v/v

Purpose

Antiseptic

Use(s)

Hand Sanitizer to help reduce bacteria that potentially can cause disease. For use when soap and water are not available.

Warnings

For External use only. Flammable. Keep away from heat or flame

Do not use

- in children less than 2 months of age

- on open skin wounds

When using this product

keep out of eyes, ears and mouth. In case of contact with eyes, rise eyes thoroughly with water.

Stop use and ask a doctor

if irritation or rash occurs. These may be signs of a serious condition.

Keep out of reach of children.

If swallowed, get medical help or contact a Poison Control Center right away.

Directions

- Place enough product on hands to cover all surfaces. Rub hands together until dry.

- Supervise children 6 years of age when using this product to avoid swallowing.

Other Information

- Store between 10-30 °C (59-85°F)

- Avoid freezing and excessive heat above 40°C (104°F)

Inactive ingredients

glycerin, hydrogen peroxide, purified water USP